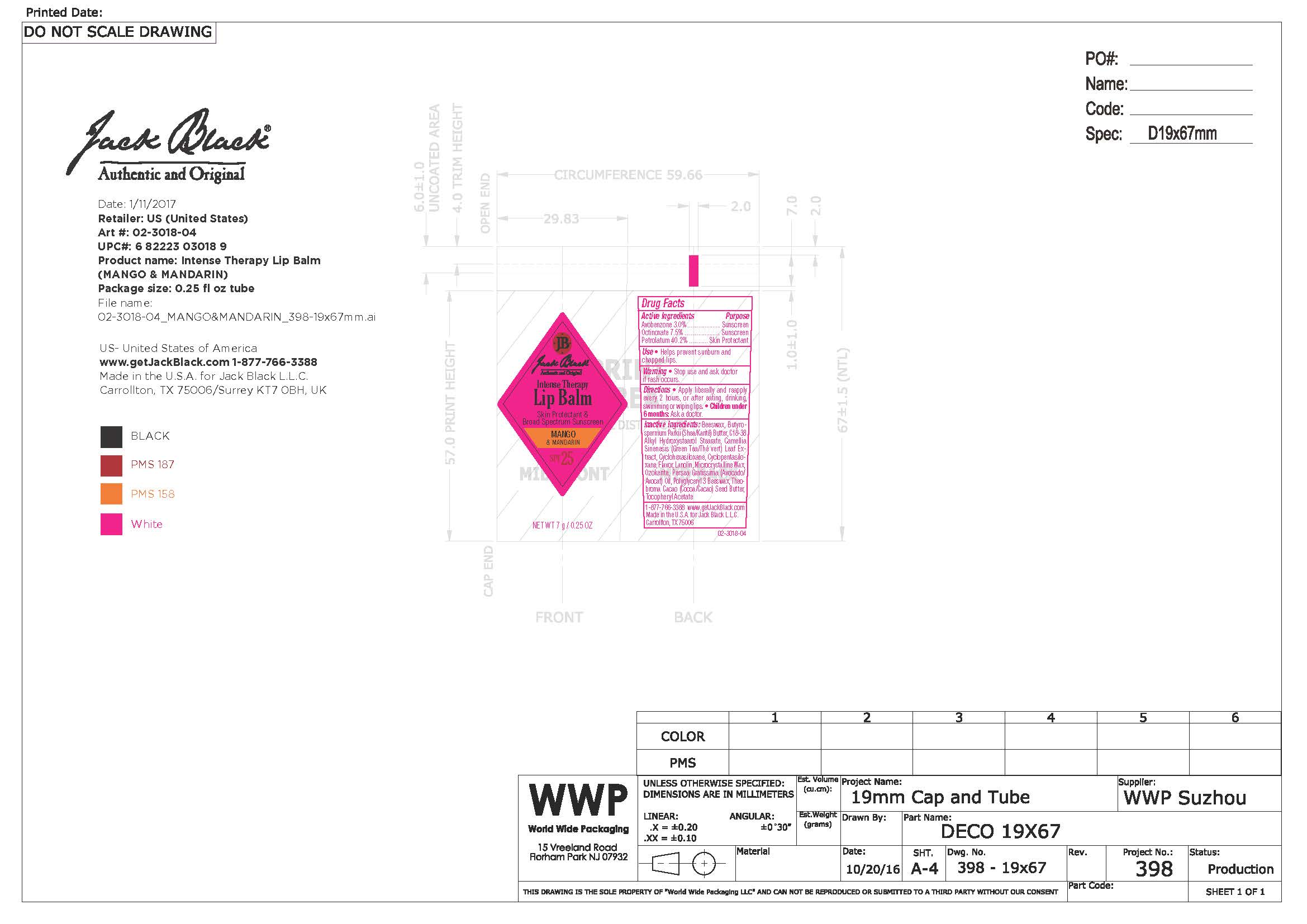 DRUG LABEL: Intense Therapy Lip Balm Mango and Mandarin
NDC: 66738-034 | Form: OINTMENT
Manufacturer: Jack Black, LLC
Category: otc | Type: HUMAN OTC DRUG LABEL
Date: 20231109

ACTIVE INGREDIENTS: OCTINOXATE 75 g/1000 g; AVOBENZONE 30 g/1000 g; PETROLATUM 402 g/1000 g
INACTIVE INGREDIENTS: CYCLOMETHICONE 5; CYCLOMETHICONE 6; GREEN TEA LEAF; SHEA BUTTER; WHITE WAX; MICROCRYSTALLINE WAX; .ALPHA.-TOCOPHEROL ACETATE; CERESIN; AVOCADO OIL; METHYL SALICYLATE

Intense Therapy Lip Balm Mango and Mandarin

Warnings

Stop use and ask doctor if rash occurs. Children under 6 months: Ask a doctor

Active Ingredients

Avobenzone 3.0% Sunscreen

Octinoxate 7.5% Sunscreen

Petrolatum 40.2% Skin Protectant

Directions

Apply liberally and reapply every 2 hours or after eating, drinking, swimming or wiping lips.

Keep out of Reach of Children

Uses

Helps prevent sunburn and chapped lips.

Uses

Helps prevent sunburn and chapped lips.

Inactive Ingredients

beeswax, butyrospermum Parkii (shea) butter, C18-38 alkyl hydroxystearol stearate, camellia sinenesis (green tea) leaf extract, cyclohexasiloxane, cyclopentasiloxane, flavor, lanolin, microcrystalline wax, ozokerite, persea gratissima (avocado) oil, ployglyceryl 3 beeswax, theobroma cacao (cocoa) seed butter, tocopheryl acetate

Questions

www.getjackblack.com

1-877-766-3388